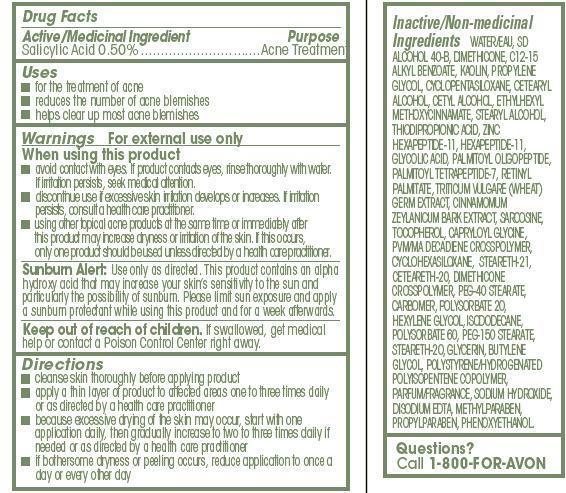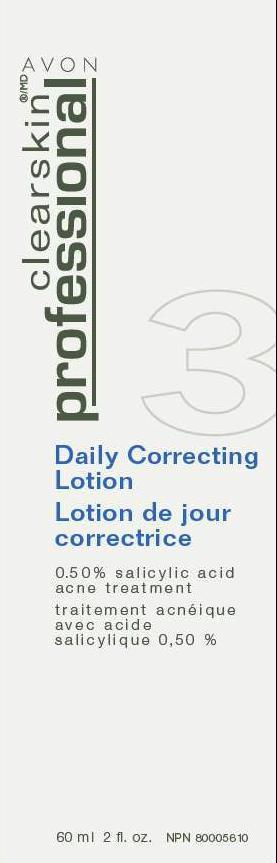 DRUG LABEL: Clearskin
NDC: 10096-0154 | Form: LOTION
Manufacturer: New Avon LLC
Category: otc | Type: HUMAN OTC DRUG LABEL
Date: 20190101

ACTIVE INGREDIENTS: SALICYLIC ACID	 5 mg/1 mL
INACTIVE INGREDIENTS: WATER

CLEARSKIN DAILY CORRECTING LOTION

Active/Medicinal Ingredient
Salicylic Acid 0.50%..............................

Purpose
...............Acne Treatment

Uses

- for the treatment of acne
- reduces the number of acne blemishes
- helps clear up most acne blemishes

Warnings

For external use only

When using this product

- avoid contact with eyes. If product contacts eyes, rinse thoroughly with water.If irritation persists, seek medical attention.
- discontinue use if excessive skin irritation develops or increases. If irritationpersists, consult a health care practitioner.
- using other topical acne products at the same time or immediately afterthis product may increase dryness or irritation of the skin. If this occurs,only one product should be used unless directed by a health care practitioner

WARNINGS AND PRECAUTIONS

Sunburn Alert: Use only as directed. This product contains an alpha hydroxy acid that may increase your skin’s sensitivity to the sun and particularly the possibility of sunburn. Please limit sun exposure and apply a sunburn protectant while using this product and for a week afterwards.

Keep out of reach of children. If swallowed, get medical help or contact a Poison Control Center right away.

Directions

- cleanse skin thoroughly before applying product
- apply a thin layer of product to affected areas one to three times daily or as directed by a health care practitioner
- because excessive drying of the skin may occur, start with one application daily, then gradually increase to two to three times daily if needed or as directed by a health care practitioner
- if bothersome dryness or peeling occurs, reduce application to once a day or every other day

Inactive/Non-medicinal
Ingredients WATER/EAU, SD ALCOHOL 40-B, DIMETHICONE, C12-15 ALKYL BENZOATE, KAOLIN, PROPYLENE GLYCOL, CYCLOPENTASILOXANE, CETEARYL ALCOHOL, CETYL ALCOHOL, ETHYLHEXYL
METHOXYCINNAMATE, STEARYL ALCOHOL, THIODIPROPIONIC ACID, ZINC HEXAPEPTIDE-11, HEXAPEPTIDE-11, GLYCOLIC ACID, PALMITOYL OLIGOPEPTIDE, PALMITOYL TETRAPEPTIDE-7, RETINYL PALMITATE, TRITICUM VULGARE (WHEAT) GERM EXTRACT, CINNAMOMUM ZEYLANICUM BARK EXTRACT, SARCOSINE, TOCOPHEROL, CAPRYLOYL GLYCINE, PVM/MA DECADIENE CROSSPOLYMER, CYCLOHEXASILOXANE, STEARETH-21, CETEARETH-20, DIMETHICONE CROSSPOLYMER, PEG-40 STEARATE, CARBOMER, POLYSORBATE 20, HEXYLENE GLYCOL, ISODODECANE, POLYSORBATE 60, PEG-150 STEARATE, STEARETH-20, GLYCERIN, BUTYLENE GLYCOL, POLYSTYRENE/HYDROGENATED POLYISOPENTENE COPOLYMER, PARFUM/FRAGRANCE, SODIUM HYDROXIDE, DISODIUM EDTA, METHYLPARABEN, PROPYLPARABEN, PHENOXYETHANOL.

Questions?
Call 1-800-FOR-AVON